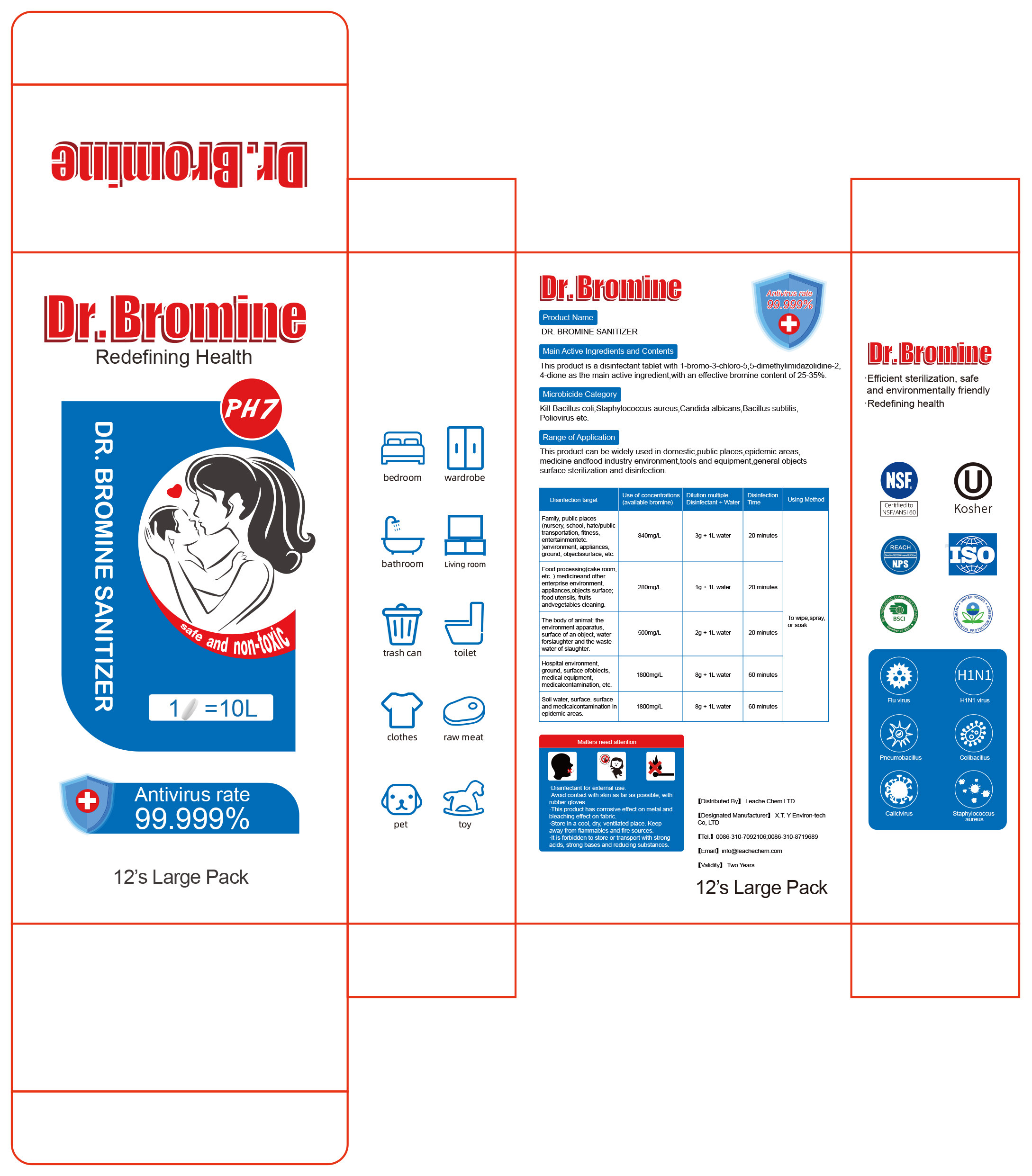 DRUG LABEL: Dr. Bromine
NDC: 86179-001 | Form: GRANULE
Manufacturer: LEACHE CHEM LTD
Category: otc | Type: HUMAN OTC DRUG LABEL
Date: 20200611

ACTIVE INGREDIENTS: 1-BROMO-3-CHLORO-5,5-DIMETHYL-2,4-IMIDAZOLIDINEDIONE 26 g/100 g
INACTIVE INGREDIENTS: CITRIC ACID MONOHYDRATE; SODIUM CHLORIDE

DOSAGE AND ADMINISTRATION

Store in a cool, dry, ventilated place.

INACTIVE INGREDIENT

Sodium Chloride & Citric Acid

INDICATIONS AND USAGE

Please follow the instructions on the package

ACTIVE INGREDIENT

1-BROMO-3-CHLORO-5,5-DIMETHYL-2,4-IMIDAZOLIDINEDIONE

keep out of reach of children

PURPOSE

Disinfection
Sterilization

WARNINGS

1.Avoid contact with skin as far as possible, with rubber gloves.
2.This product has corrosive effect on metal and bleaching effect on fabric.
3.Store in a cool, dry, ventilated place. Keep away from flammables and fire sources.
4.It is forbidden to store or transport with strong acids, strong bases and reducing substances.